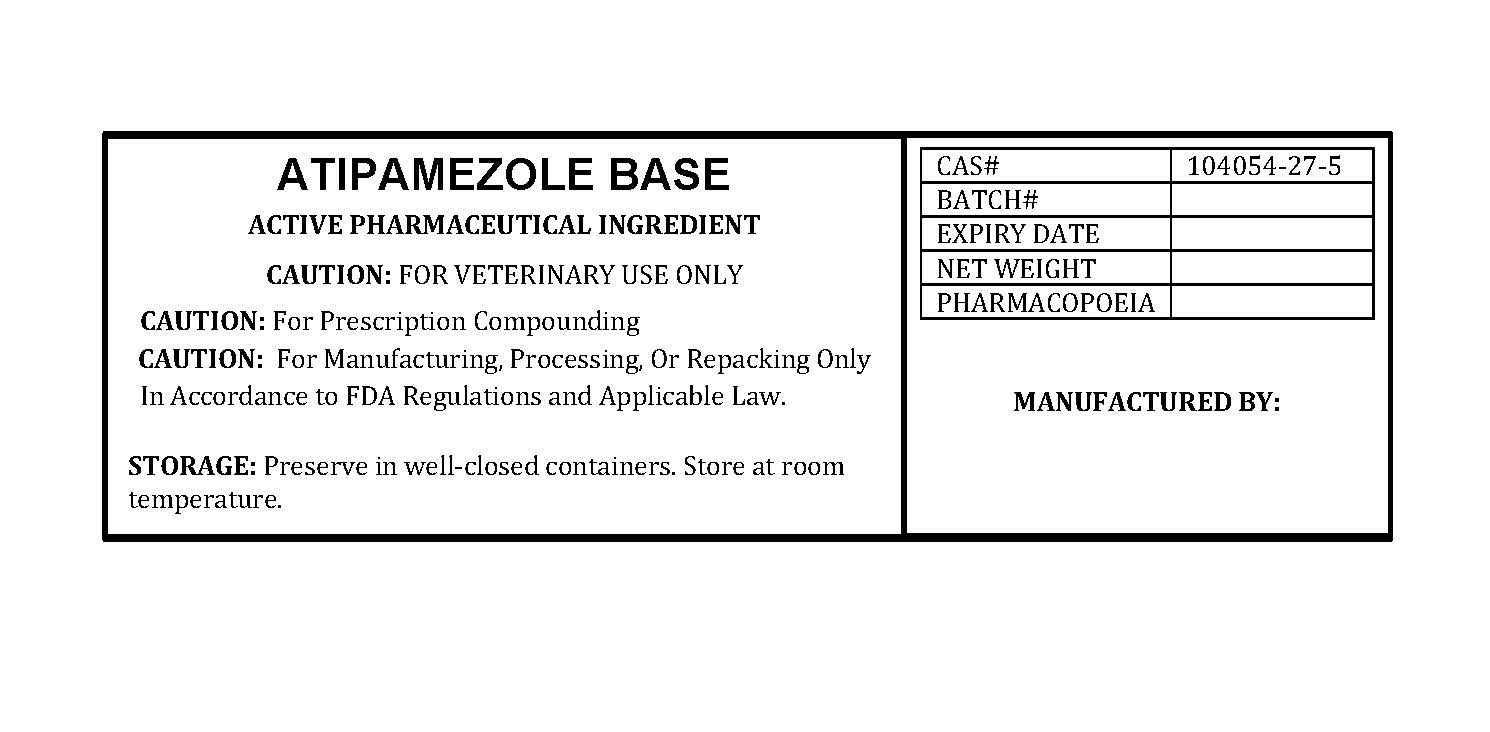 DRUG LABEL: ATIPAMEZOLE
NDC: 86184-006 | Form: POWDER
Manufacturer: MAEDA INC
Category: other | Type: BULK INGREDIENT - ANIMAL DRUG
Date: 20260216

ACTIVE INGREDIENTS: ATIPAMEZOLE 1 g/1 g

ATIPAMEZOLE

PACKAGE LABEL

atipamezolebaselabelfile.jpg